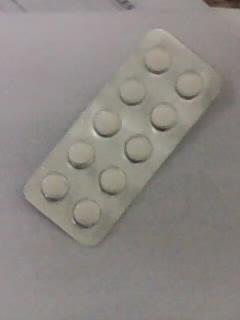 DRUG LABEL: APHENAP
NDC: 46084-041 | Form: TABLET
Manufacturer: A P J Laboratories Limited
Category: otc | Type: HUMAN OTC DRUG LABEL
Date: 20140102

ACTIVE INGREDIENTS: DIPHENHYDRAMINE HYDROCHLORIDE 25 mg/1 1
INACTIVE INGREDIENTS: CELLULOSE, MICROCRYSTALLINE 30 mg/1 1; STARCH, CORN 15 mg/1 1; POVIDONE K30 10 mg/1 1; METHYLPARABEN 1 mg/1 1; TITANIUM DIOXIDE 1 mg/1 1; MAGNESIUM STEARATE 10 mg/1 1; TALC 15 mg/1 1; SODIUM STARCH GLYCOLATE TYPE A POTATO 20 mg/1 1; SILICON DIOXIDE 1 mg/1 1

active ingredient

DIPHENHYDRAMINE HYDROCHLORIDE

purpose

Antihistamine

keep out of reach of children

In case of overdose, get medical help or contact a Poison Control Center right away(1-800-222-1222).

uses

Temporarily relieves these symptoms due to hay fever or other upper respiratory allergies and common cold, sneezing, runny nose, itchy, watery eyes, itchy throat and nose

Ask a doctor before use if you have glaucoma, a breathing problem such as emphysema or chronic bronchitis, trouble urinating due to an enlarged prostate gland.

directions

Adults and children 12 years and over: take 25 to 50 mg (1 to 2 tablet) every 4 to 6 hours; not more than 12 tablets in 24 hours.
Children 6 years to 12 years of age: take 25 mg (1 tablet) every 4 to 6 hours; not more than 6 tablets in 24 hours.
Children under 6 years of age: ask a doctor

inactive ingredient

CELLULOSE, MICROCRYSTALLINE

INACTIVE INGREDIENT

MAGNESIUM STEARATE

INACTIVE INGREDIENT

METHYLPARABEN

INACTIVE INGREDIENT

POVIDONE K30

INACTIVE INGREDIENT

SILICON DIOXIDE

INACTIVE INGREDIENT

SODIUM STARCH GLYCOLATE TYPE A POTATO

INACTIVE INGREDIENT

STARCH, CORN

INACTIVE INGREDIENT

TALC

INACTIVE INGREDIENT

TITANIUM DIOXIDE